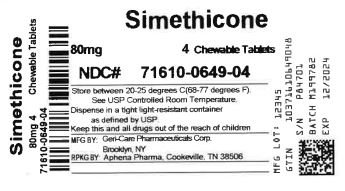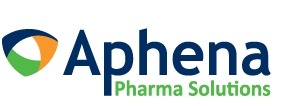 DRUG LABEL: SIMETHICONE
NDC: 71610-649 | Form: TABLET, CHEWABLE
Manufacturer: Aphena Pharma Solutions - Tennessee, LLC
Category: otc | Type: HUMAN OTC DRUG LABEL
Date: 20250110

ACTIVE INGREDIENTS: DIMETHICONE 80 mg/1 1
INACTIVE INGREDIENTS: CELLULOSE, MICROCRYSTALLINE; DEXTRATES; SILICON DIOXIDE; TRICALCIUM PHOSPHATE; STARCH, CORN; CROSPOVIDONE; MAGNESIUM STEARATE; SUCRALOSE

gc 791

Active ingredient (in each tablet)

Simethicone 80 mg

Purpose

Anti-Gas

Uses

relieves pressure, bloating, and fullness
commonly referred to as gas

Warnings

If pregnant or breast feeding,ask a health professional before use.

Keep out of reach of children.

Directions

- chew or crush tablet completely before swallowing
- adults and children 12 years and over: take 1-2 tablets as needed after meals and at bedtime.

Do not exceed 6 tablets in 24 hours except under the advice and supervision of a doctor.

- children under 12 years: ask a doctor

Other information

- each tablet contains: calcium 65 mg
- Tamper Evident: Do not use if imprinted seal under cap is missing or broken
- store at room temperature, 15°C - 30°C (59˚F - 86˚F)
- protect from moisture

HOW SUPPLIED

Simethicone Chewable Tablets, 80 mg are white, round, tablets, debossed with "44 & 137" on one side and are supplied as:

NDC 57896-791-01 in bottle of 100 chewable tablets

NDC 57896-791-08 in bottle of 80 chewable tablets

Distributed by:

GERI-CARE Pharmaceuticals Corp.

1650 63rd Street, Brooklyn, NY 11204

Inactive ingredients

cellulose, corn starch, crospovidone, dextrates hydrated, flavor,
magnesium stearate, silica, sucralose, calcium phosphate.

Questions or comments?

1-800-540-3765

Repackaging Information

Please reference the How Suppliedsection listed above for a description of individual tablets. This drug product has been received by Aphena Pharma - TN in a manufacturer or distributor packaged configuration and repackaged in full compliance with all applicable cGMP regulations. The package configurations available from Aphena are listed below:

Count | 80 mg
4 | 71610-649-04

Store between 20°-25°C (68°-77°F). See USP Controlled Room Temperature. Dispense in a tight light-resistant container as defined by USP. Keep this and all drugs out of the reach of children.

Repackaged by:
Cookeville, TN 38506
20220519JK

PRINCIPAL DISPLAY PANEL - 80 mg

NDC 71610-649 - Simethicone 80 mg Chewable Tablet - Rx Only